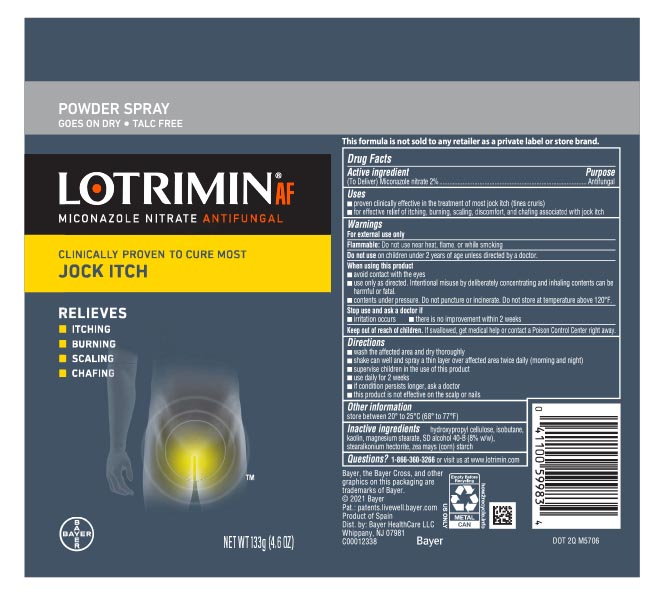 DRUG LABEL: Lotrimin
NDC: 11523-0133 | Form: AEROSOL, POWDER
Manufacturer: Bayer Healthcare LLC.
Category: otc | Type: HUMAN OTC DRUG LABEL
Date: 20251204

ACTIVE INGREDIENTS: MICONAZOLE NITRATE 20 mg/1 g
INACTIVE INGREDIENTS: STEARALKONIUM HECTORITE; STARCH, CORN; MAGNESIUM STEARATE; KAOLIN; ISOBUTANE

Lotrimin® AF Jock Itch Powder Spray Talc Free

Drug Facts

Active ingredient

Miconazole nitrate 2%

Purpose

Antifungal

Uses

- proven clinically effective in the treatment of most jock itch (tinea cruris)
- for effective relief of itching, burning, scaling and discomfort, and chafing associated with jock itch

Warnings

For external use only

Flammable: Do not use while smoking or near heat or flame

For external use only

Flammable: DO not use near heat, flame, or while smoking

Do not use on children under 2 years of age unless directed by a doctor

When using this product

- avoid contact with the eyes
- use only as directed. Intentional misuse by deliberately concentrating and inhaling contents can be harmful or fatal
- contents under pressure. Do not puncture or incinerate. Do not store at temperature above 120°F.

Stop use and ask a doctor if

- irritation occurs
- there is no improvement within 2 weeks

Keep out of reach of children. If swallowed, get medical help or contact a Poison Control Center right away.

Directions

- wash affected area and dry thoroughly
- shake can well and spray a thin layer over affected area twice daily (morning and night)
- supervise children in the use of this product
- use daily for 2 weeks
- if condition persists longer, ask a doctor
- this product is not effective on the scalp or nails

Other information

store between 20° to 25°C (68° to 77°F)

Inactive ingredients

hydroxypropyl cellulose, isobutane, kaolin, magnseium stearate, SD alcohol 40-B (8% v/v), stearalkonium hectorite, zea mays (corn) starch

Questions?

1-866-360-3266

PRINCIPAL DISPLAY PANEL - 133 g Can Label

Powder Spray
goes on dry

NDC 11523-4140-2

LOTRIMIN® AF
ANTIFUNGAL
miconazole nitrate

Clinically Proven To Cure
Most Jock Itch

Relieves Itching,
Burning, Scaling
& Chafing

NET WT 133g (4.6 OZ)